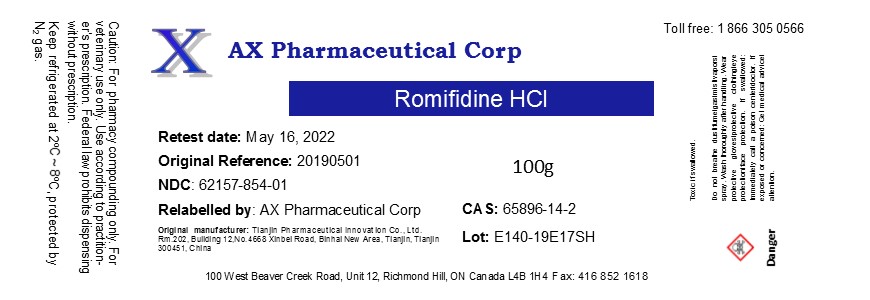 DRUG LABEL: Romifidine Hydrochloride
NDC: 62157-854 | Form: POWDER
Manufacturer: AX Pharmaceutical Corp
Category: other | Type: BULK INGREDIENT
Date: 20190604

ACTIVE INGREDIENTS: Romifidine Hydrochloride 1 g/1 g

Romifidine Hydrochloride